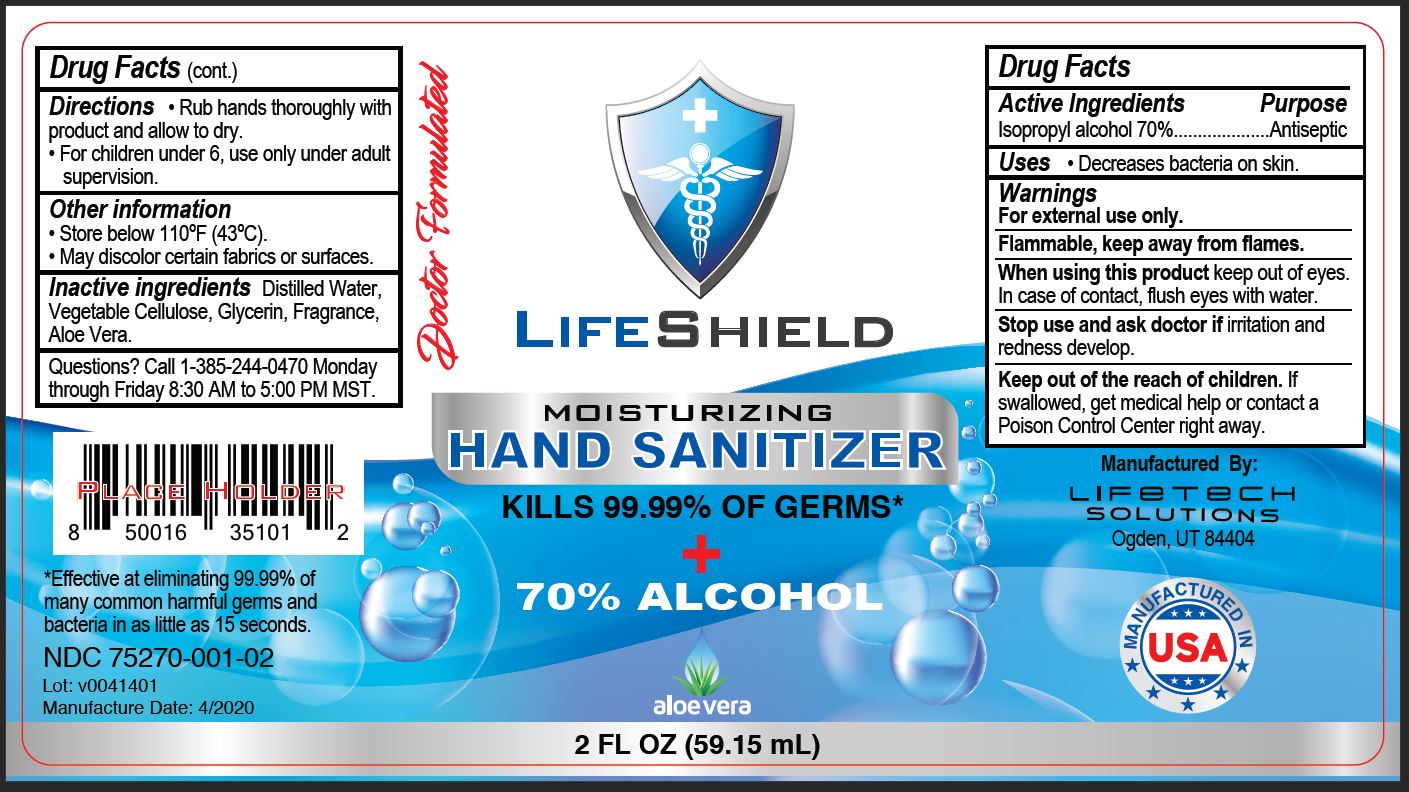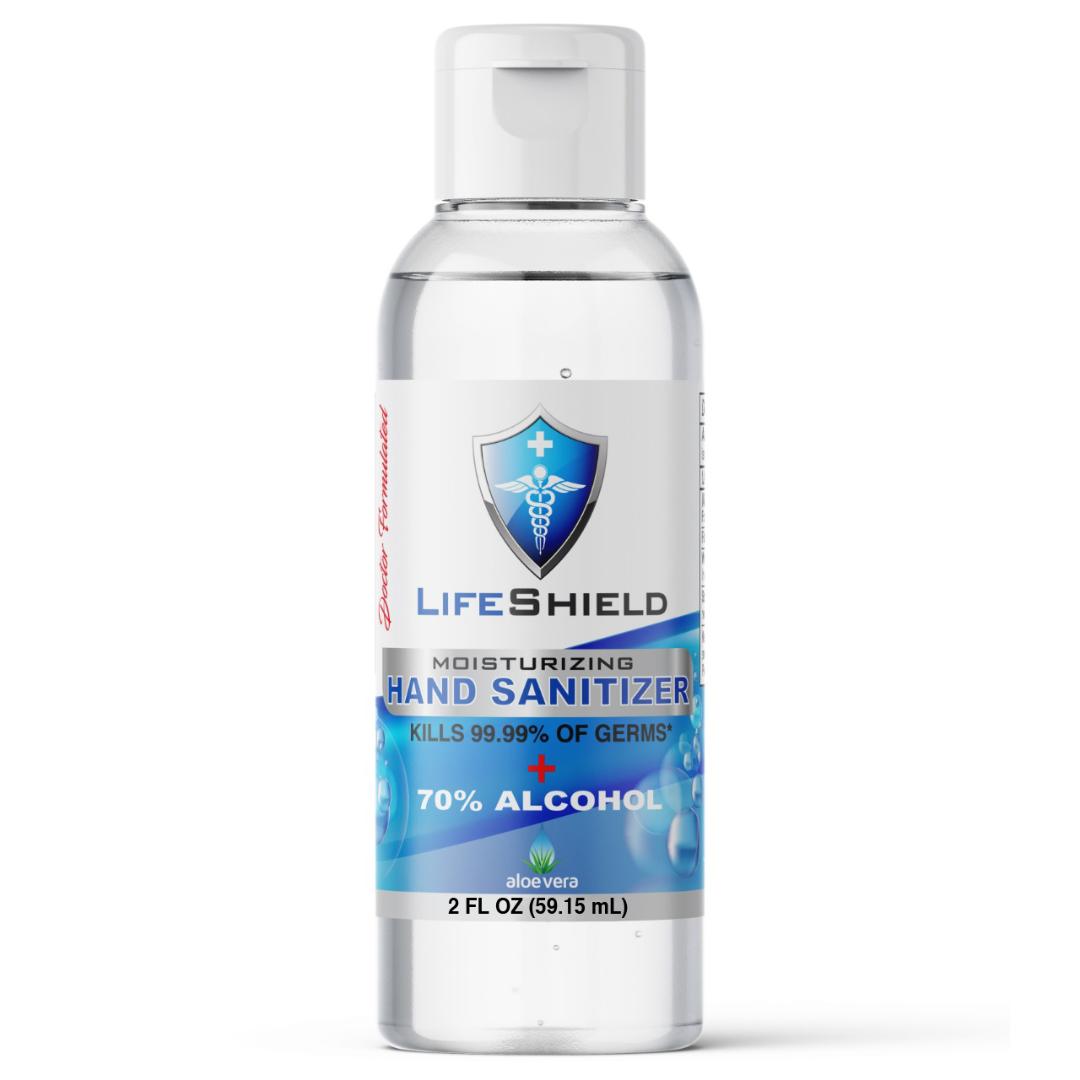 DRUG LABEL: LifeShield 2oz Hand Sanitizer
NDC: 75270-101 | Form: GEL
Manufacturer: LifeTech Pharma LLC.
Category: otc | Type: HUMAN OTC DRUG LABEL
Date: 20200413

ACTIVE INGREDIENTS: ALCOHOL 37.34 g/52.6 g
INACTIVE INGREDIENTS: LIMONENE, (+)- 0.053 g/52.6 g; ALOE VERA LEAF POLYSACCHARIDES 0.053 g/52.6 g; GLYCERIN 0.368 g/52.6 g; WATER 14.04 g/52.6 g; HYDROXYPROPYL CELLULOSE, UNSPECIFIED 0.736 g/52.6 g

Hand Sanitizer

This hand Sanitizer was manufactured according to the Federal Register 21 CFR 310, utilizing:

a. USP/FCC grade Isopropyl alcohol (70% v/v)

b. Distilled/purified water

c. Hydroxypropylcellulose (as Vegetable Cellulose)

d. Glycerin USP/FCC grade

e. Limonene (as fragrance)

f. Aloe Vera extract

Hand Sanitizer Label:

Active Ingredient(s)

Isopropyl alcohol 70%

Purpose

Antiseptic, Hand Sanitizer

Uses

Decreases bacteria on skin.

Warnings

For external use only. Flammable, keep away from flames.

When using this product keep out of eyes. In case of contact, flush eyes with water.

Stop use

Stop use and ask doctor if irritation and redness develop.

KEEP OUT OF REACH OF CHILDREN

Keep out of the reach of children. If swallowed, get medical help or contact a Poison Control Center right away.

Directions

• Rub hands thoroughly with product and allow to dry.
• For children under 6, use only under adult supervision.

Other information

• Store below 110ºF (43ºC).
• May discolor certain fabrics or surfaces.

Inactive ingredients

Inactive ingredients Distilled Water,
Structured Silver, Vegetable Cellulose,
Glycerin, Aloe Vera, Fragrance.

Questions

Questions? Call 1-385-244-0470 Monday
through Friday 8:30 AM to 5:00 PM MST.

Package Label - Principal Display Panel

2 FL OZ (59.15 mL) NDC: 75270-001-02